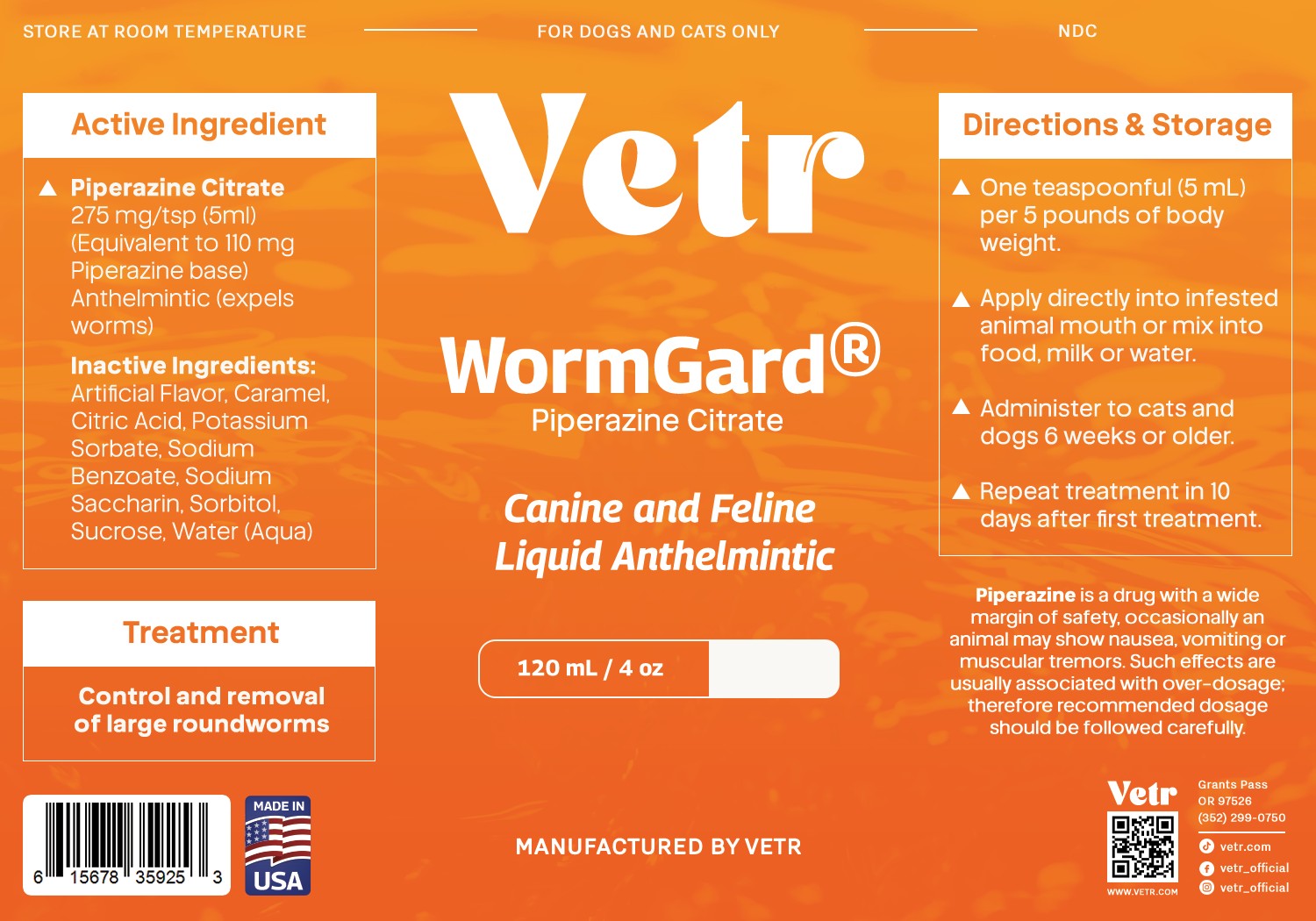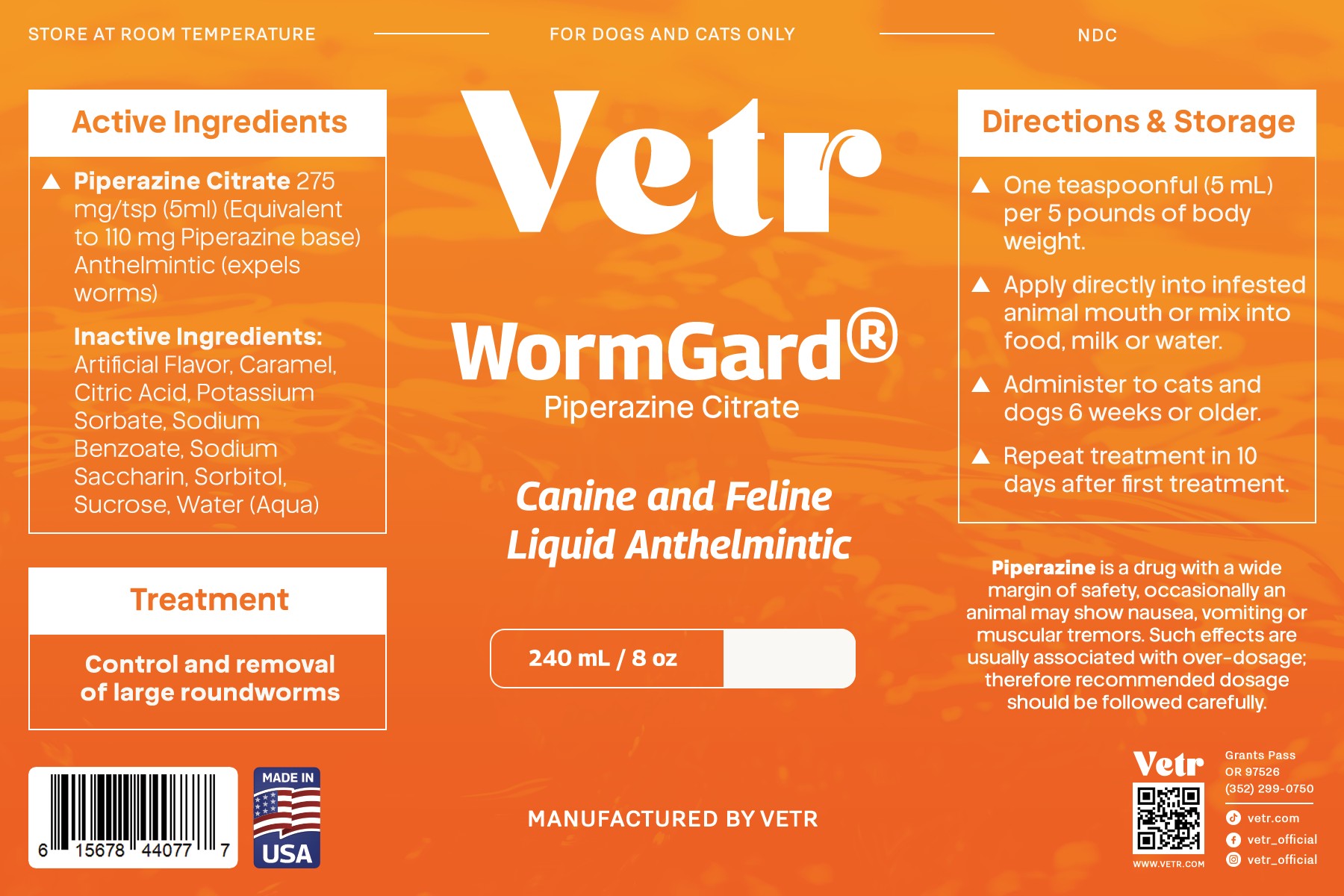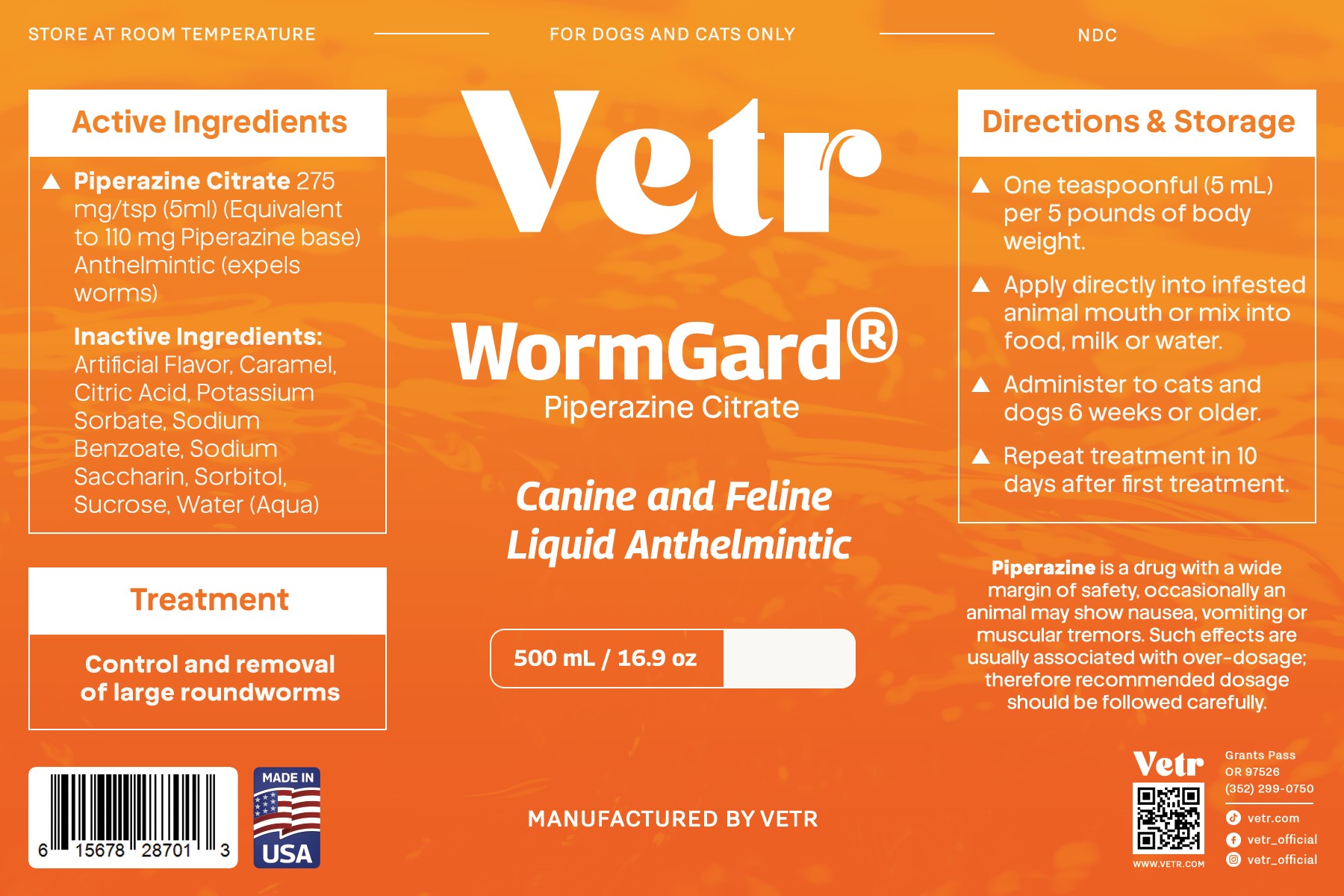 DRUG LABEL: WormGard
NDC: 86213-791 | Form: LIQUID
Manufacturer: Vetr, LLC
Category: animal | Type: OTC ANIMAL DRUG LABEL
Date: 20251120

ACTIVE INGREDIENTS: PIPERAZINE CITRATE 22 mg/1 mL
INACTIVE INGREDIENTS: CITRIC ACID; POTASSIUM SORBATE; SODIUM BENZOATE; SODIUM SACCHARIN; SORBITOL; SUCROSE; WATER

WormGard; piperazine citrate liquid (2.2% piperazine base)

WARNINGS AND PRECAUTIONS

Although Piperazine is a drug with a wide margin of safety. Occasionally
an animal may show nausea, vomiting, or muscular tremors. Such side
effects are usually associated with over-dosage: Therefore, recommended
dosage should be followed carefully.

- Animals with known kidney pathology should be treated only by a veterinarian.
- For Oral Animal Use Only.
- KEEP OUT OF REACH OF CHILDREN

Consult veterinarian before using in severely debilitated animals. Do not worm animals more than twice yearly except as advised by a veterinarian. This product is effective for those roundworm stages found in the intestine and does not remove migrating larval stages. Animals
should be checked periodically by a veterinarian or the presence of other intestinal parasites

Directions for Use.

- One teaspoonful (5 ml) per 5 pounds of body weight.
- Applied directly into infested animal mouth or mixed into food, milk or water.
- Administer to cats and dogs 6 weeks or older.
- Repeat treatment in 10 days after first treatment

STORAGE AND HANDLING

Store at room temperature

ACTIVE INGREDIENT

piperazine citrate 275 mg/5 mL (1 teaspoonful). Equivalent to 110 mg piperazine Base per teaspoonful (2.2% piperazine base)

Inactive ingredients.

Carmel flavor, citric acid, potassium sorbate, sodium benzoate, sodium saccharin, sorbitol, sucrose, water.